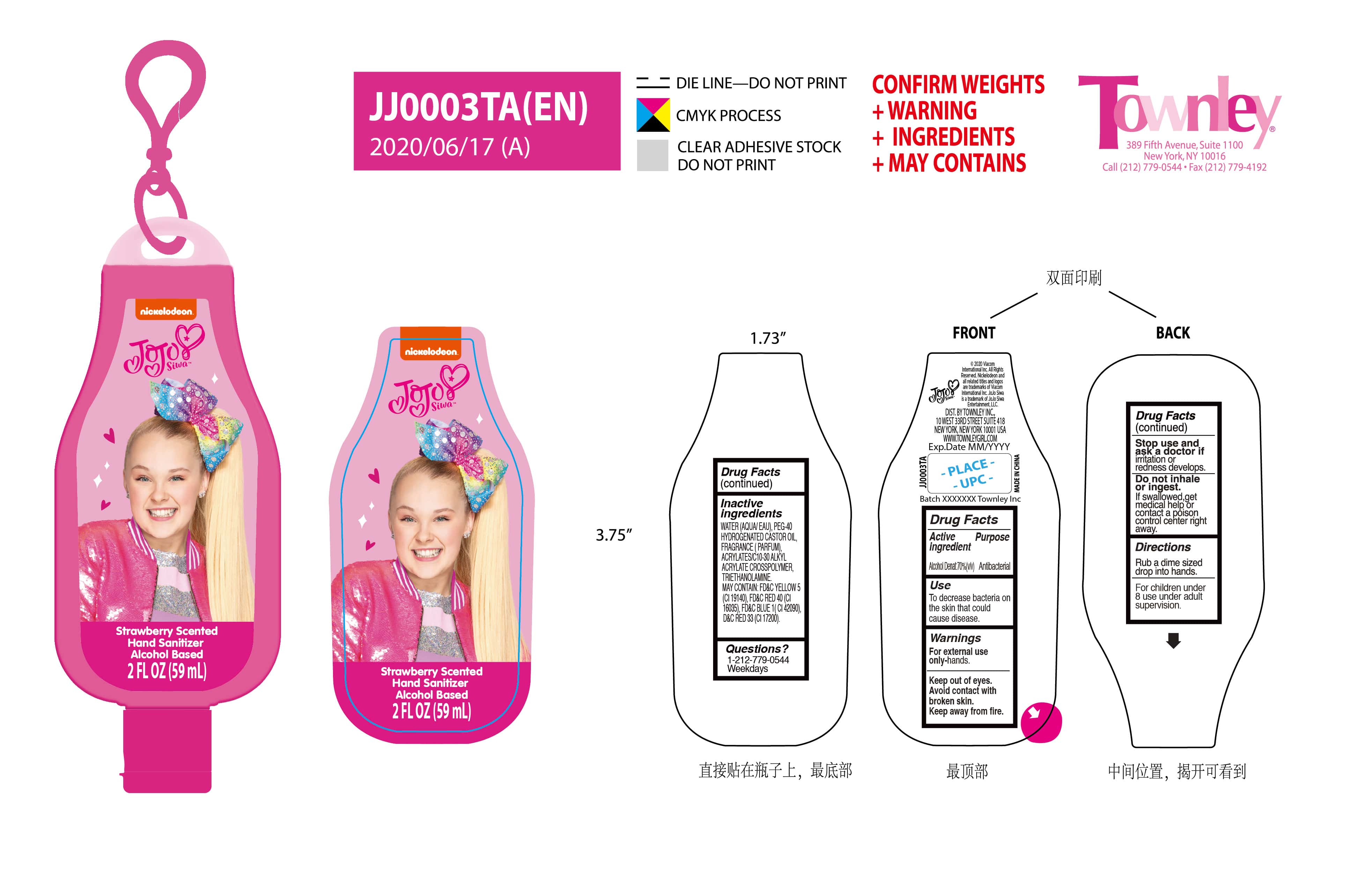 DRUG LABEL: strawberry scented hand sanitizer
NDC: 76383-074 | Form: GEL
Manufacturer: BBC GROUP LIMITED
Category: otc | Type: HUMAN OTC DRUG LABEL
Date: 20210713

ACTIVE INGREDIENTS: ALCOHOL 70 mL/100 mL
INACTIVE INGREDIENTS: WATER 36.2397 g/100 mL; FD&C RED NO. 40 0.0003 g/100 mL; TROLAMINE 0.16 g/100 mL; STRAWBERRY 0.2 g/100 mL; CARBOMER INTERPOLYMER TYPE A (ALLYL SUCROSE CROSSLINKED) 0.2 mL/100 mL; POLYOXYL 40 HYDROGENATED CASTOR OIL 0.2 mL/100 mL

JJ0003TA (EN) rose, strawberry
BBC

Active ingredient .............purpose

alcohol Denate: 70%(v/v)..... Antibacterial

Use

To decrease bacteria on the skin that could cause disease.

Warnings

For external use only-hands

keep out of eyes- avoid contact with broken skin.

Keep away from fire.

Stop use and ask a dosctor if irritation or radness develops

Do not inhale or ingest. If swallowed, get medical help or contact a poison control right away.

Direction

Rub a dime sized drop into hands.

For children under 8 use under adult supervision

Inactive ingredients

INACTIVE INGREDIENTS: WATER(AQUA/EAU), PEG-40 HYDROGENATED CASTOR OIL, FRAGRANCE(PARFUM), ACRYLATES/ c10-30 ALKYL ACRYLATE CROSSPOLYMER, TRIETHANOLAMINE.
MAY CONTAIN: FD&C RED 40, D&C RED 33, FD&C BLUE 1, FD&C YELLOW 5.

Questions?

1-212-779-0544 weekdays